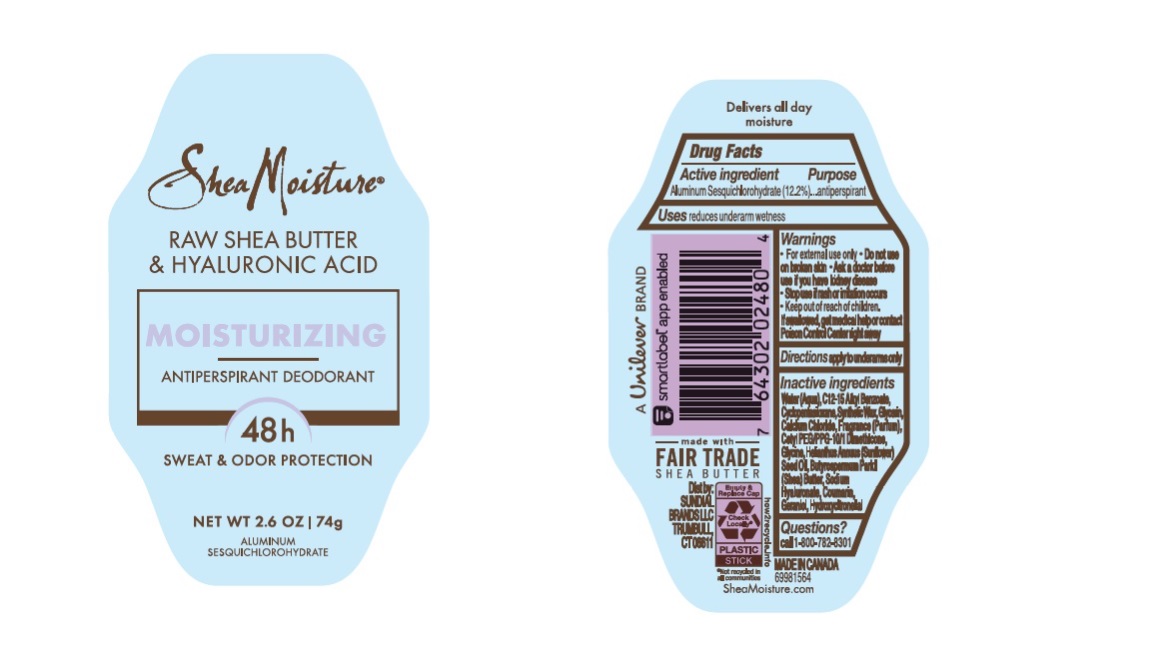 DRUG LABEL: Dove
NDC: 64942-2147 | Form: STICK
Manufacturer: Conopco Inc. d/b/a/ Unilever
Category: otc | Type: HUMAN OTC DRUG LABEL
Date: 20241024

ACTIVE INGREDIENTS: ALUMINUM SESQUICHLOROHYDRATE 12.2 g/100 g
INACTIVE INGREDIENTS: CALCIUM CHLORIDE; WATER; ALKYL (C12-15) BENZOATE; CYCLOMETHICONE 5; SYNTHETIC WAX (1200 MW); GLYCERIN; CETYL PEG/PPG-10/1 DIMETHICONE (HLB 4); GLYCINE; SUNFLOWER OIL; SHEA BUTTER; HYALURONATE SODIUM; GERANIOL; HYDROXYCITRONELLAL; COUMARIN

Shea Moisture Raw Shea Butter & Hyaluronic Acid Moisturizing 48h Antiperspirant Deodorant

Drug Facts

Active ingredient

Aluminum Sesquichlorohydrate (12.2)

Purpose

antiperspirant

Uses

reduces underarm wetness

Warnings

• For external use only.
• Do not use on broken skin .
• Ask a doctor before use if you have kidney disease.
• Stop use if rash or irritation occurs.

• Keep out of reach of children.

If swallowed, get medical help or contact a Poison Control Center right away.

Directions

apply to underarms only

Inactive ingredients

Water (Aqua), C12-15 Alkyl Benzoate, Cyclopentasiloxane, Synthetic Wax, Glycerin, Calcium Chloride, Fragrance (Parfum), Cetyl PEG/PPG-10/1 Dimethicone, Glycine, Helianthus Annuus (Sunflower) Seed Oil, Butyrospermum Parkii (Shea) Butter, Sodium Hyaluronate, Coumarin, Geraniol, Hydroxycitronellal.

Questions?

Call 1-800-761-3683